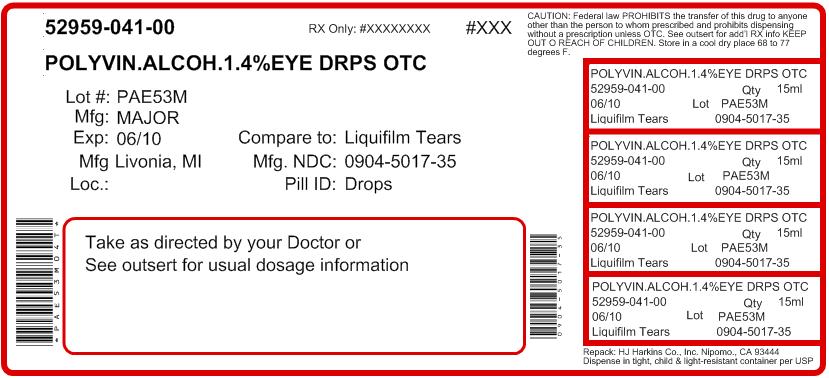 DRUG LABEL: LiquiTears
NDC: 52959-041 | Form: SOLUTION/ DROPS
Manufacturer: H.J. Harkins Company, Inc.
Category: otc | Type: HUMAN OTC DRUG LABEL
Date: 20120309

ACTIVE INGREDIENTS: POLYVINYL ALCOHOL 14 mg/1 mL
INACTIVE INGREDIENTS: SODIUM PHOSPHATE, DIBASIC; EDETATE DISODIUM; SODIUM PHOSPHATE, MONOBASIC; SODIUM CHLORIDE; WATER; BENZALKONIUM CHLORIDE

Artificial Tears Solution Drug Facts

Active ingredient

Polyvinyl Alcohol 1.4%

Purpose

Lubricant

Uses

- to prevent further irritation
- to relieve dryness of the eye

Warnings

- Do not use if solution changes color or becomes cloudy

When using this product

- do not touch tip of container to any surface to avoid contamination
- replace cap after use

Stop use and ask a doctor if

- you experience eye pain, changes in vision, continued redness or irritation of the eye
- condition worsens or persists for more than 72 hours

Keep out of reach of children.

If swallowed, get medical help or contact a Poison Control Center right away

Directions

- instill 1 to 2 drops in the affected eye(s) as needed

Other information

- store at 15° - 30°C (59° - 86°F)
- keep tightly closed

Inactive ingredients

dibasic sodium phosphate, edetate disodium, monobasic sodium phosphate, sodium chloride,

purified water. Phosphoric acid and/or sodium hydroxide may be added to adjust pH. PRESERVATIVE ADDED: benzalkonium chloride 0.01%

Questions ?

Serious side effects associated with use of this product may be reported to 1800-323-0000

*MAJOR LIQUITEARS IS NOT MANUFACTURED OR DISTRIBUTED BY ALLERGAN, INC. OWNER OF THE REGISTERED TRADEMARK, LIQUIFILM TEARS®.

Package/Label Principal Display Panel

MAJOR®

NDC 0904-5017-35

LiquiTears

Polyvinyl Alcohol 1.4%

Lubricant Eye Drops (Sterile)

Relieves Burning due to Dryness of the Eye

Compare to Active Ingredient of Liquifilm Tears®*

1/2 FL. OZ. (15 mL)

Repacked by:
H.J. Harkins Company, Inc.
Grover Beach, CA 93433